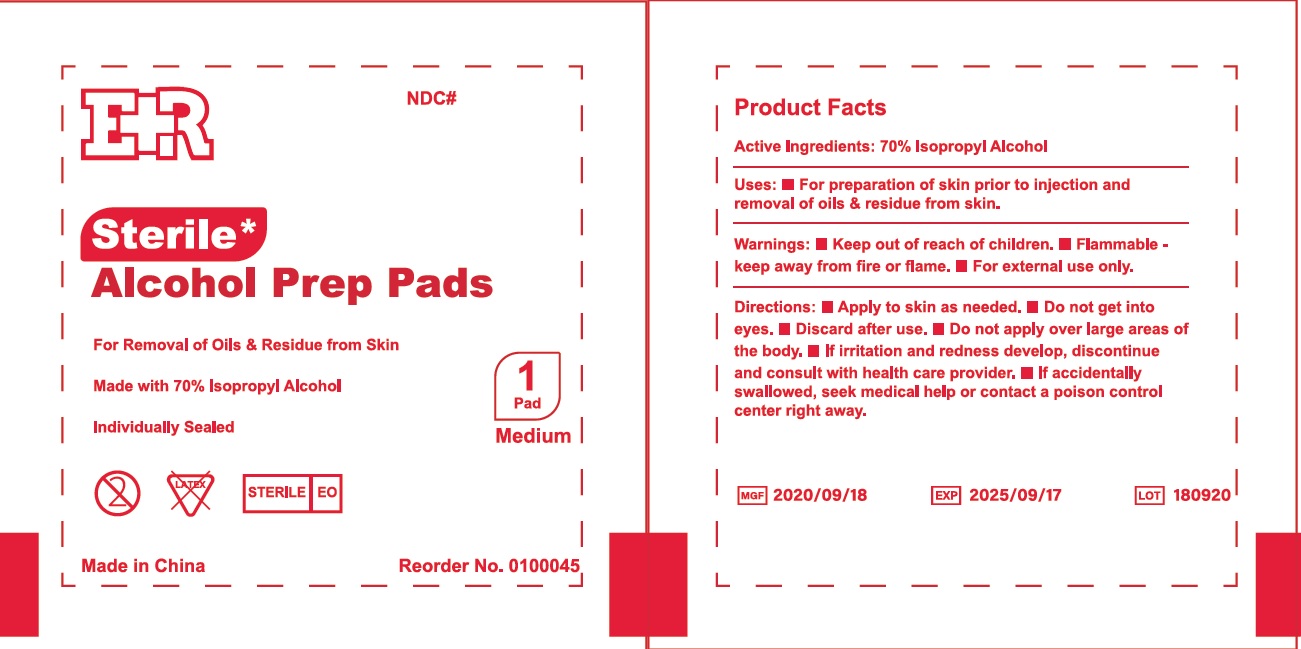 DRUG LABEL: Sterile Alcohol Prep Pads
NDC: 72766-101 | Form: SWAB
Manufacturer: Yangzhou Suxiang Medical Instrument Co., Ltd.
Category: otc | Type: HUMAN OTC DRUG LABEL
Date: 20230809

ACTIVE INGREDIENTS: ISOPROPYL ALCOHOL 70 g/100 g
INACTIVE INGREDIENTS: WATER

Sterile Alcohol Prep Pads

Active Ingredient

Isopropyl Alcohol, 70% v/v

Purpose

Antiseptic

Uses

For preparation of skin prior to injection and removal of oils and residue from skin.

Warnings

Flammable - keep away from fire or flame.

For external use only.

Do Not Use

In the eyes

Stop Use and ask a doctor if

Irritation and redness develops

If condition persists for more than 72 hours, consult a physician

Discontinue use and consult a healthcare practitioner if

Irritation develops

Keep out of reach of children

If swallowed, get medical help or contact a Poison Control Center right away

Directions

- apply to skin as needed
- Do not get into eyes.
- Discard after use.
- Do not apply large areas of the body.
- If irritation and redness develop, discontinue and consult with health care provider.
- If accidentallhy swallowed, seek medical help or contact a poison control center right away.

Other Information

Store at room temperature 15°-30°C (59°-86°F)

Avoid excessive heat

Inactive Ingredients

Water